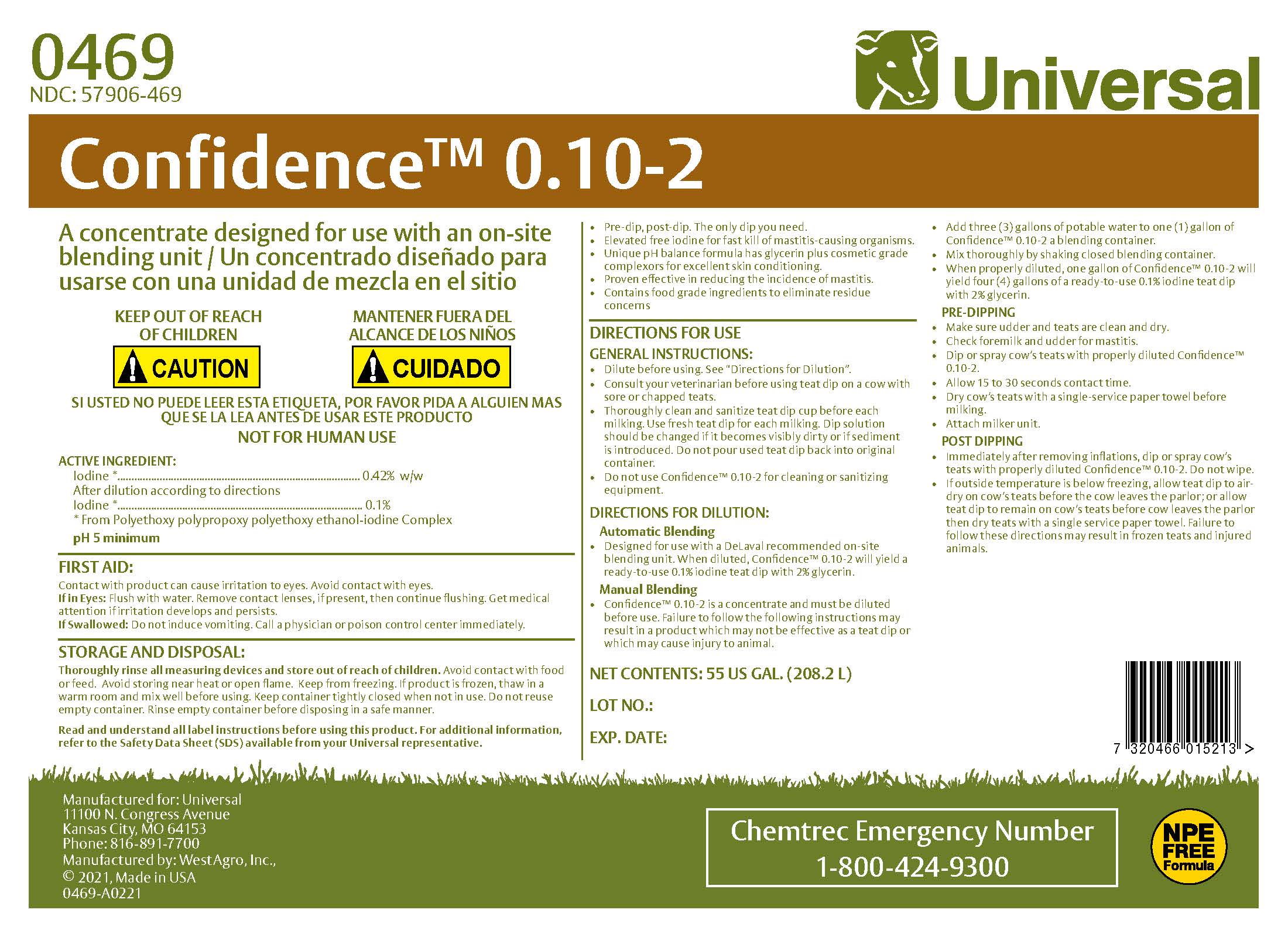 DRUG LABEL: Confidence 0.10-2
NDC: 57906-469 | Form: CONCENTRATE
Manufacturer: Universal
Category: animal | Type: OTC ANIMAL DRUG LABEL
Date: 20220121

ACTIVE INGREDIENTS: IODINE .0042 kg/1 kg
INACTIVE INGREDIENTS: WATER; GLYCERIN; XANTHAN GUM; POLOXAMER 335; ANHYDROUS CITRIC ACID; SODIUM CHLORIDE; SODIUM HYDROXIDE; SODIUM IODIDE; DOCUSATE SODIUM; SODIUM IODATE

Universal
Confidence 0.10-2

WARNINGS AND PRECAUTIONS

Confidence™ 0.10-2

A concentrate designed for use with an on-site blending unit / Un concentrado diseñado para usarse con una unidad de mezcla en el sitio

SI USTED NO PUEDE LEER ESTA ETIQUETA, POR FAVOR PIDA A ALGUIEN MAS QUE SE LA LEA ANTES DE USAR ESTE PRODUCTO

NOT FOR HUMAN USE

ACTIVE INGREDIENT:

Iodine * ................................... 0.42% w/w

After dilution according to directions

Iodine * .................................. 0.1%

* From Polyethoxy polypropoxy polyethoxy ethanol-iodine Complex

pH 5 minimum

FIRST AID:

Contact with product can cause irritation to eyes. Avoid contact with eyes.

If in Eyes: Flush with water. Remove contact lenses, if present, then continue flushing. Get medical attention if irritation develops and persists.

If Swallowed: Do not induce vomiting. Call a physician or poison control center immediately.

STORAGE AND DISPOSAL:

Thoroughly rinse all measuring devices and store out of reach of children. Avoid contact with food or feed. Avoid storing near heat or open flame. Keep from freezing. If product is frozen, thaw in a warm room and mix well before using. Keep container tightly closed when not in use. Do not reuse empty container. Rinse empty container before disposing in a safe manner.

GENERAL PRECAUTIONS

Read and understand all label instructions before using this product. For additional information, refer to the Safety Data Sheet (SDS) available from your Universal representative.

PURPOSE

- Pre-dip, post-dip. The only dip you need.
- Elevated free iodine for fast kill of mastitis-causing organisms.
- Unique pH balance formula has glycerin plus cosmetic grade complexors for excellent skin conditioning.
- Proven effective in reducing the incidence of mastitis.
- Contains food grade ingredients to eliminate residue concerns

INDICATIONS AND USAGE

DIRECTIONS FOR USE

GENERAL INSTRUCTIONS

- Dilute before using. See "Directions for Dilution".
- Consult your veterinarian before using teat dip on a cow with sore or chapped teats.
- Thoroughly clean and sanitize teat dip cup before each miling. Use fresh teat dip for each milking. Dip solution should be changed if it becomes visibly dirty or if sediment is introduced. Do not pour used teat dip back into original container.
- Do not use Confidence™ 0.10-2 for sanitizing equipment.

DIRECTIONS FOR DILUTION

Automatic Blending

- Designed for use with a DeLaval recommended on-site blending unit. When diluted, Confidence™ 0.10-2 will yield a ready-to-use 0.1% iodine teat dip with 2% glycerin.

Manual Blending

- Confidence™ 0.10-2 is a concentrate and must be diluted before use. Failure to follow the following instructions may result in a product which may not be effective as a teat dip or which may cause injury to animal.
- Add three (3) gallons of potable water to one (1) gallon of Confidence™ 0.10-2 to a blending container.
- Mix thoroghly by shaking closed blending container.
- When properly diluted, one gallon of Confidence™ 0.10-2 will yield four (4) gallons of a ready-to-use 0.1% iodine teat dip with 2% glycerin.

PRE-DIPPING

- Made sure udder and teats are clean and dry.
- Check foremilk and udder for mastitis.
- Dip or spray cow's teats with properly diluted Confidence™ 0.10-2.
- Allow 15 to 30 seconds contact time.
- Dry cow's teat with a single-service paper towel before milking.
- Attach milker unit.

POST DIPPING

- Immediately after removing inflations, clip or spray cow's teats with properly diluted Confidence™ 0.10-2. Do not wipe.
- If outside temperature is below freezing, allow teat dip to air-dry on cow's teats before the cow leaves the parlor; or allow teat dip to remain on cow's teats before cow leaves the parlor then dry teats with a single service paper towel. Failure to follow these directions may result in frozen teats and injured animals.

Chemtrec Emergency Number

1-800-424-9300

NPE Free Formula

NET CONTENTS: US GAL (L)

LOT NO.:

EXP. DATE: